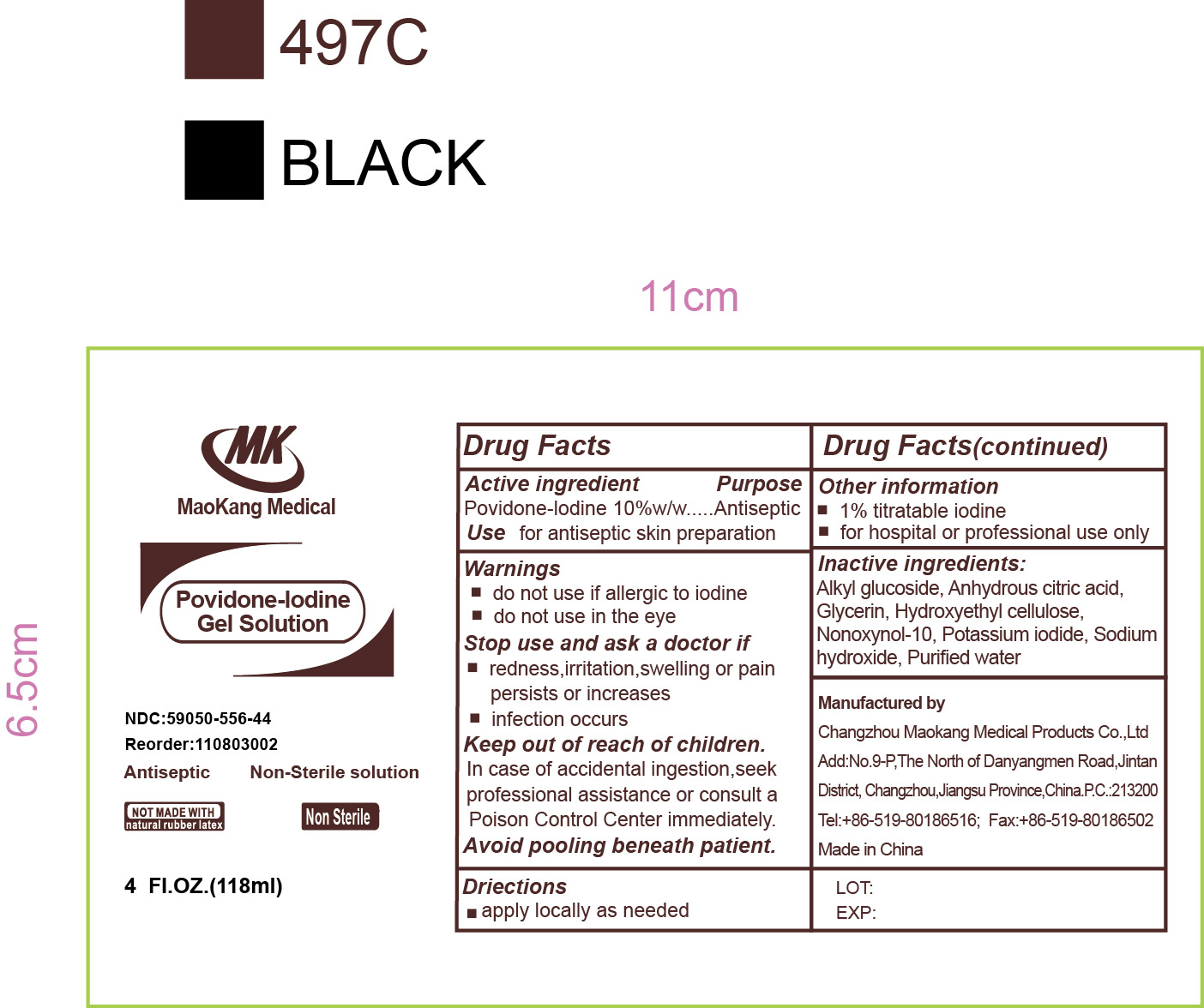 DRUG LABEL: Povidone-Iodine Gel Solution
NDC: 59050-556 | Form: SOLUTION
Manufacturer: Changzhou Moakang Medical Products Co. Ltd
Category: otc | Type: HUMAN OTC DRUG LABEL
Date: 20200629

ACTIVE INGREDIENTS: POVIDONE-IODINE 11 mg/1 mL
INACTIVE INGREDIENTS: NONOXYNOL-10; POTASSIUM IODIDE; WATER; ANHYDROUS CITRIC ACID; GLYCERIN; HYDROXYETHYL CELLULOSE (2000 MPA.S AT 1%); SODIUM HYDROXIDE

Povidone-Iodine Gel Solution

Active Ingredient

Povidone-Iodine 10%

Purpose

Antiseptic

Use

Antiseptic skin preparation

Warnings

Do not use

- if allergic to Iodine
- in the eyes

Stop use and ask doctor if

- redness, irritation, swelling or pain persists or increases
- infection occurs

Keep out of reach of children

In case of accidental ingestion, seek professional assistance or consult a poison control center immediately.

Avoid pooling beneath the patient

Ask a doctor before use if injuries are

- deep puncture wounds
- serious burns

Directions

apply locally as needed

Other Information

- 1% titratable
- for hospital or professional use only

Inactive Ingredients

alkyl glucoside, anhydrous citric acid, glycerin, hydroxyethyl cellulose, nonoxynol-10, potassium iodide, sodium hydroxide, purified water